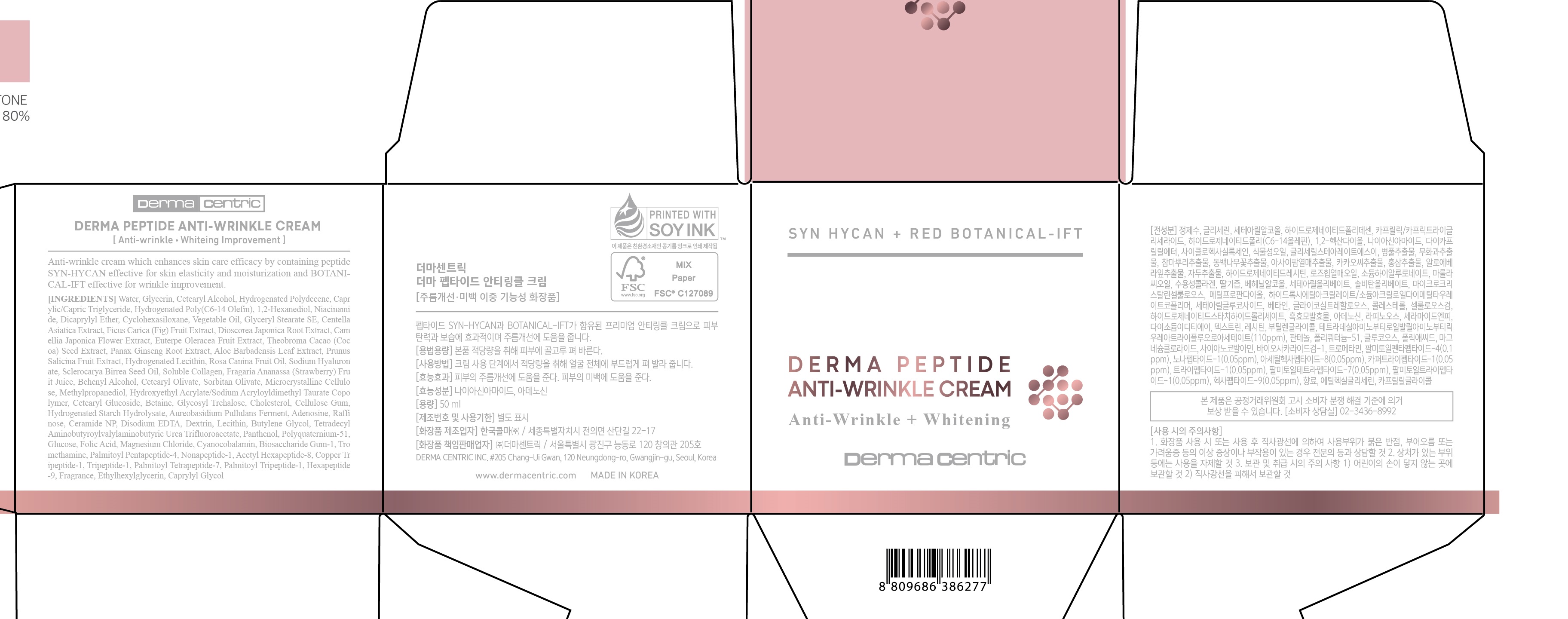 DRUG LABEL: DERMA PEPTIDE ANTI-WRINKLE AMPOULE
NDC: 79593-0006 | Form: LIQUID
Manufacturer: DERMA CENTRIC INC
Category: otc | Type: HUMAN OTC DRUG LABEL
Date: 20210328

ACTIVE INGREDIENTS: ADENOSINE 0.044 g/100 mL; NIACINAMIDE 2 g/100 mL
INACTIVE INGREDIENTS: WATER; GLYCERIN

ACTIVE INGREDIENT

niacinamide, adenosine

PURPOSE

anti-wrinkle, whitening improvement

KEEP OUT OF REACH OF THE CHILDREN

WARNINGS

■ For external use only.

■ Do not use in eyes.

■ lf swallowed, get medical help promptly.

■ Stop use, ask doctor lf irritation occurs.

■ Keep out of reach of children.

DOSAGE AND ADMINISTRATION

for external use only

INACTIVE INGREDIENT

WATER
METHYLPROPANEDIOL
GLYCERIN
1,2-HEXANEDIOL
GLYCERIN
WATER
MAGNESIUM CHLORIDE
TETRADECYL AMINOBUTYROYLVALYLAMINOBUTYRIC UREA TRIFLUOROACETATE
BETAINE
WATER
DIPROPYLENE GLYCOL
GLYCERIN
LAMINARIA JAPONICA EXTRACT
ECLIPTA PROSTRATA LEAF EXTRACT
FRUCTOOLIGOSACCHARIDES
1,2-HEXANEDIOL
HYDROGENATED LECITHIN
BETA-GLUCAN
HYDROLYZED HYALURONIC ACID
NIACINAMIDE
DIGLYCERIN
WATER
POLYQUATERNIUM-51
1,2-HEXANEDIOL
GLYCOSYL TREHALOSE
HYDROGENATED STARCH HYDROLYSATE
WATER
OCTYLDODECETH-16
GLYCERIN
METHYLPROPANEDIOL
WATER
POLYQUATERNIUM-51
PIPER METHYSTICUM LEAF/ROOT/STEM EXTRACT
HYDROGENATED LECITHIN
BETA-GLUCAN
PANAX GINSENG BERRY EXTRACT
CENTELLA ASIATICA EXTRACT
1,2-HEXANEDIOL
XANTHAN GUM
TROMETHAMINE
CARBOMER
WATER
BUTYLENE GLYCOL
HYDROGENATED LECITHIN
PANTHENOL
RAFFINOSE
1,2-HEXANEDIOL
FOLIC ACID
CHOLESTEROL
CERAMIDE NP
TROMETHAMINE
PALMITOYL PENTAPEPTIDE-4
ETHYLHEXYLGLYCERIN
TOCOPHEROL
CARBOMER
CELLULOSE GUM
ADENOSINE
FRAGRANCE
DISODIUM EDTA
SODIUM HYALURONATE
DEXTRIN
THEOBROMA CACAO (COCOA) SEED EXTRACT
GLYCERIN
WATER
LEUCOJUM AESTIVUM BULB EXTRACT
WATER
GLYCERIN
1,2-HEXANEDIOL
SOLUBLE COLLAGEN
MALTODEXTRIN
RUBUS FRUTICOSUS (BLACKBERRY) LEAF EXTRACT
CYANOCOBALAMIN
PERSEA GRATISSIMA (AVOCADO) FRUIT EXTRACT
MALTODEXTRIN
LEPIDIUM MEYENII ROOT EXTRACT
MALTODEXTRIN
HYDROLYZED LUPINE PROTEIN
METHYLPROPANEDIOL
ALOE BARBADENSIS LEAF EXTRACT
FRAGARIA ANANASSA (STRAWBERRY) FRUIT JUICE
PRUNUS SALICINA FRUIT EXTRACT
HELIANTHUS ANNUUS (SUNFLOWER) SEED OIL
TUBER MAGNATUM EXTRACT

INDICATIONS AND USAGE

apply proper amount to the skin